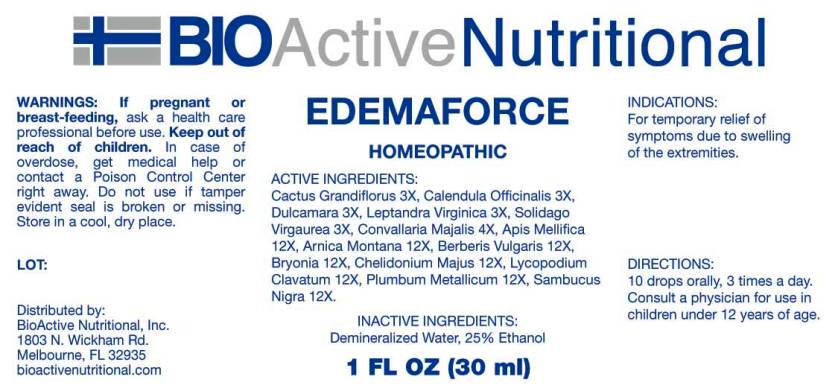 DRUG LABEL: Edemaforce
NDC: 43857-0395 | Form: LIQUID
Manufacturer: BioActive Nutritional, Inc.
Category: homeopathic | Type: HUMAN OTC DRUG LABEL
Date: 20160531

ACTIVE INGREDIENTS: SELENICEREUS GRANDIFLORUS STEM 3 [hp_X]/1 mL; CALENDULA OFFICINALIS FLOWERING TOP 3 [hp_X]/1 mL; SOLANUM DULCAMARA TOP 3 [hp_X]/1 mL; VERONICASTRUM VIRGINICUM ROOT 3 [hp_X]/1 mL; SOLIDAGO VIRGAUREA FLOWERING TOP 3 [hp_X]/1 mL; CONVALLARIA MAJALIS 4 [hp_X]/1 mL; APIS MELLIFERA 12 [hp_X]/1 mL; ARNICA MONTANA 12 [hp_X]/1 mL; BERBERIS VULGARIS ROOT BARK 12 [hp_X]/1 mL; BRYONIA ALBA ROOT 12 [hp_X]/1 mL; CHELIDONIUM MAJUS 12 [hp_X]/1 mL; LYCOPODIUM CLAVATUM SPORE 12 [hp_X]/1 mL; LEAD 12 [hp_X]/1 mL; SAMBUCUS NIGRA FLOWERING TOP 12 [hp_X]/1 mL
INACTIVE INGREDIENTS: WATER; ALCOHOL

Drug Facts:

ACTIVE INGREDIENTS:

Cactus Grandiflorus 3X, Calendula Officinalis 3X, Dulcamara 3X, Leptandra Virginica 3X, Solidago Virgaurea 3X, Convallaria Majalis 4X, Apis Mellifica 12X, Arnica Montana 12X, Berberis Vulgaris 12X, Bryonia (Alba) 12X, Chelidonium Majus 12X, Lycopodium Clavatum 12X, Plumbum Metallicum 12X, Sambucus Nigra 12X.

INDICATIONS:

For temporary relief of symptoms due to swelling of the extremities.

WARNINGS:

If pregnant or breast-feeding, ask a health care professional before use.

Keep out of reach of children. In case of overdose, get medical help or contact a Poison Control Center right away.

Do not use if tamper evident seal is broken or missing.

Store in cool, dry place.

Keep out of reach of children. In case of overdose, get medical help or contact a Poison Control Center right away.

DIRECTIONS:

10 drops orally, 3 times a day. Consult a physician for use in children under 12 years of age.

INDICATIONS:

For temporary relief of symptoms due to swelling of the extremities.

INACTIVE INGREDIENTS:

Demineralized Water, 25% Ethanol

QUESTIONS:

Distributed by:
BioActive Nutritional, Inc.
1803 N. Wickham Rd.
Melbourne, FL 32935
bioactivenutritional.com

PACKAGE LABEL DISPLAY:

BIOActive Nutritional

EDEMAFORCE

HOMEOPATHIC

1 FL OZ (30 ml)